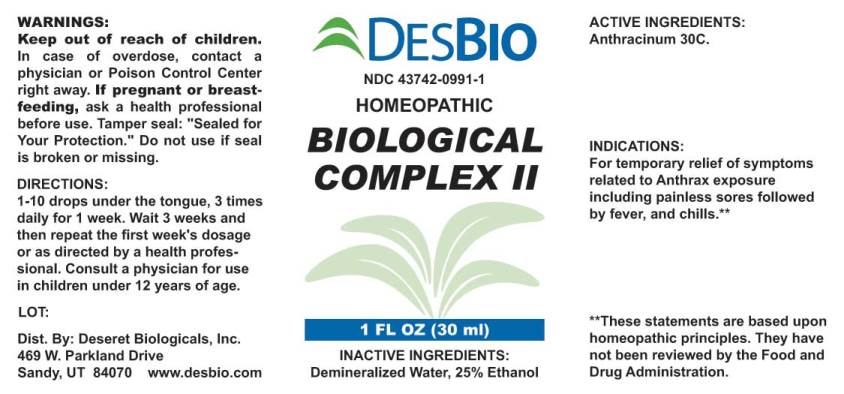 DRUG LABEL: Biological Complex
NDC: 43742-0991 | Form: LIQUID
Manufacturer: Deseret Biologicals, Inc.
Category: homeopathic | Type: HUMAN OTC DRUG LABEL
Date: 20170309

ACTIVE INGREDIENTS: BACILLUS ANTHRACIS IMMUNOSERUM RABBIT 30 [hp_C]/1 mL
INACTIVE INGREDIENTS: WATER; ALCOHOL

Drug Facts:

ACTIVE INGREDIENTS:

Anthracinum 30C.

INDICATIONS:

For temporary relief of symptoms related to Anthrax exposure including painless sores followed by fever, and chills.**

**These statements are based upon homeopathic principles. They have not been reviewed by the Food and Drug Administration.

WARNINGS:

Keep out of reach of children. In case of overdose, contact physician or Poison Control Center right away.

If pregnant or breast-feeding, seek advice of a health professional before use.

Tamper seal: "Sealed for Your Protection." Do not use if seal is broken or missing.

Keep out of reach of children. In case of overdose, contact physician or Poison Control Center right away.

DIRECTIONS:

1-10 drops under the tongue, 3 times daily for 1 week. Wait 3 weeks and then repeat the first weeks dosage or as directed by a health professional. Consult a physician for use in children under 12 years of age.

INDICATIONS:

For temporary relief of symptoms related to Anthrax exposure including painless sores followed by fever, and chills.**

**These statements are based upon homeopathic principles. They have not been reviewed by the Food and Drug Administration.

INACTIVE INGREDIENTS:

Demineralized Water, 25% Ethanol.

QUESTIONS:

Dist. By: Deseret Biologicals, Inc.
469 W. Parkland Drive
Sandy, UT 84070 www.desbio.com

PACKAGE LABEL DISPLAY:

DESBIO

NDC 43742-0991-1

HOMEOPATHIC

BIOLOGICAL

COMPLEX II

1 FL OZ (30 ml)